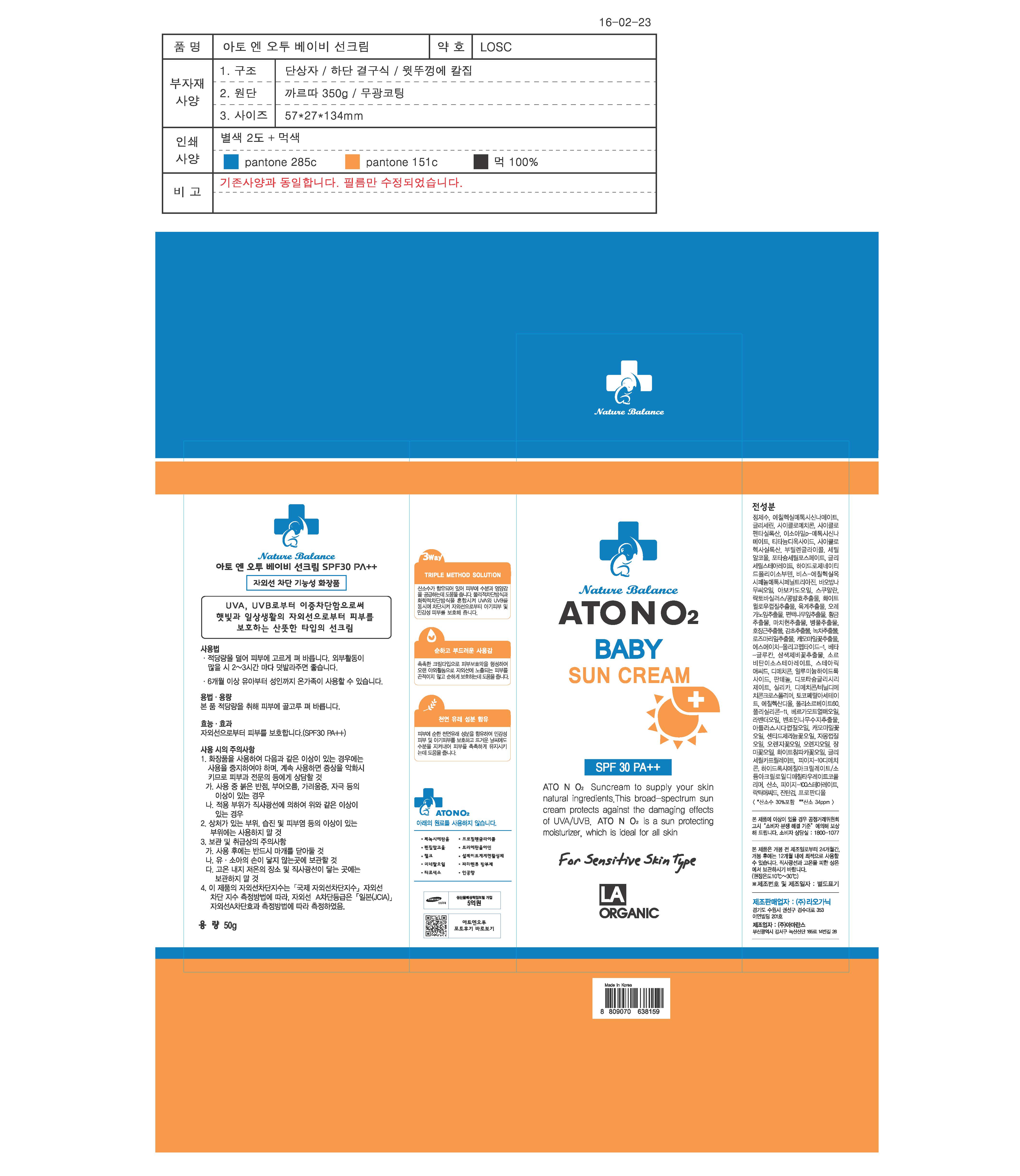 DRUG LABEL: ATONO2 Baby Sun Cream
NDC: 70993-0003 | Form: CREAM
Manufacturer: LAORGANIC Co., Ltd.
Category: otc | Type: HUMAN OTC DRUG LABEL
Date: 20161012

ACTIVE INGREDIENTS: TITANIUM DIOXIDE 2.97 g/100 g; OCTINOXATE 7 g/100 g
INACTIVE INGREDIENTS: GLYCERIN

Drug Facts

ACTIVE INGREDIENT

Ethylhexyl Methoxycinnamate, Titanium Dioxide

INACTIVE INGREDIENT

Glycerin, Cyclomethicone, Cyclopentasiloxane, Isoamyl p-methoxycinnamate, Cyclohexasiloxane, Butylene Glycol, Cetyl Alcohol, Potassium Cetyl Phosphate, Glyceryl Stearate, Hydrogenated Polyisobutene, Bis-Ethylhexyloxyphenol Methoxyphenyl, Triazine, PEG-10 Dimethicone, Dimethicone, PEG-100 Stearate, etc.

PURPOSE

Skin Protectant - Sunscreen

keep out of reach of the children

INDICATIONS AND USAGE

Apply proper amount to the skin

WARNINGS

- For external use only
- When using this product

1. If any one of following symptoms occurs when using cosmetics, stop using it and consult a dermatologist.
A. red spot, swelling, itching, stimulus
B. symptoms mentioned above are caused by sunlight.

2. Do not apply on skin where there is wound, eczema, or irritation.

3. Storage and cautions for handling
A. Close stopper after using.
B. Keep out of reach of children.
C. Keep away from high or low temperature and direct sunlight.

4. This is not a medicinal product. Made of 100% cosmetic ingredients, it is a sensitive-skin care product for all skin types.

DOSAGE AND ADMINISTRATION

for external use only